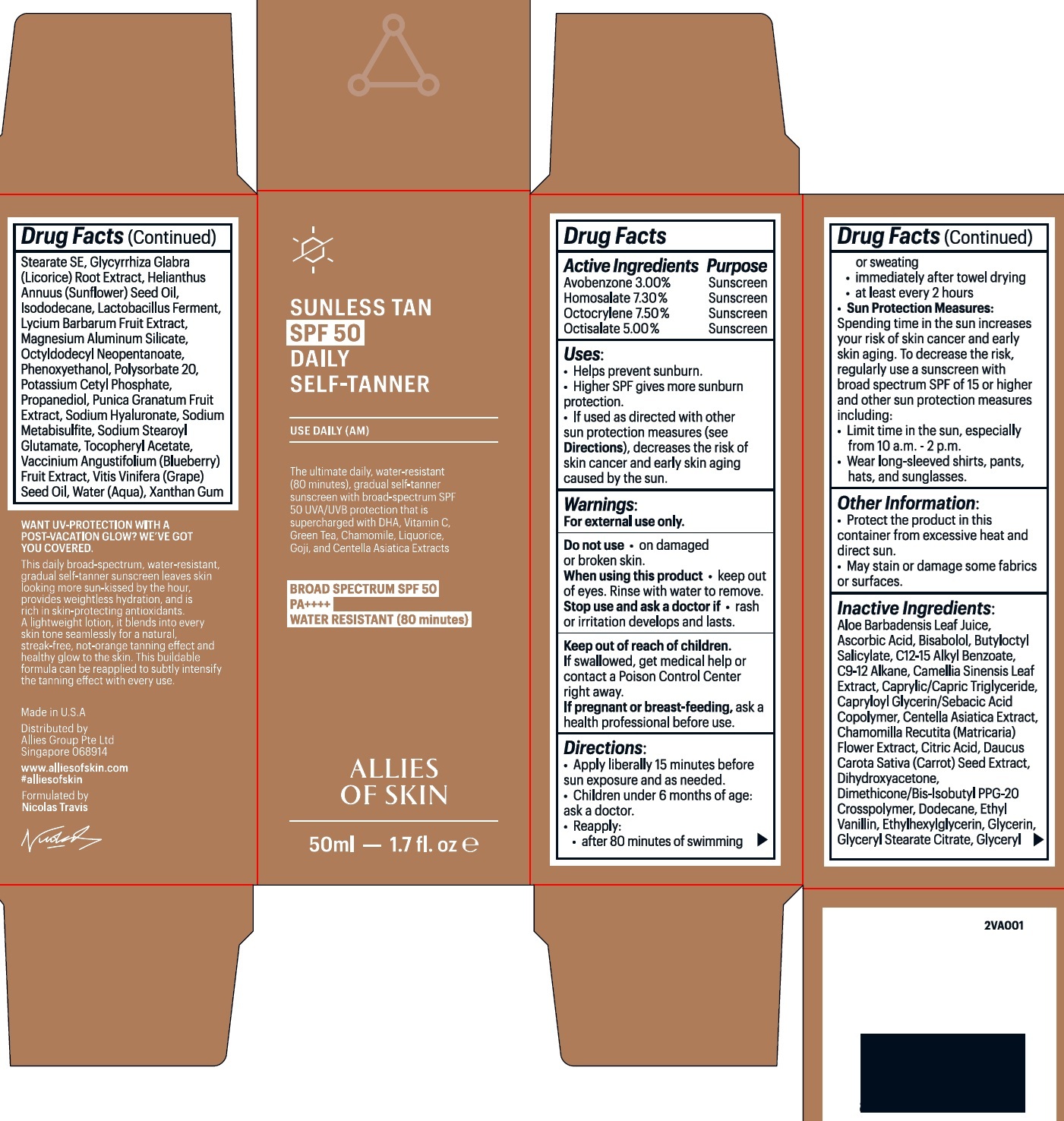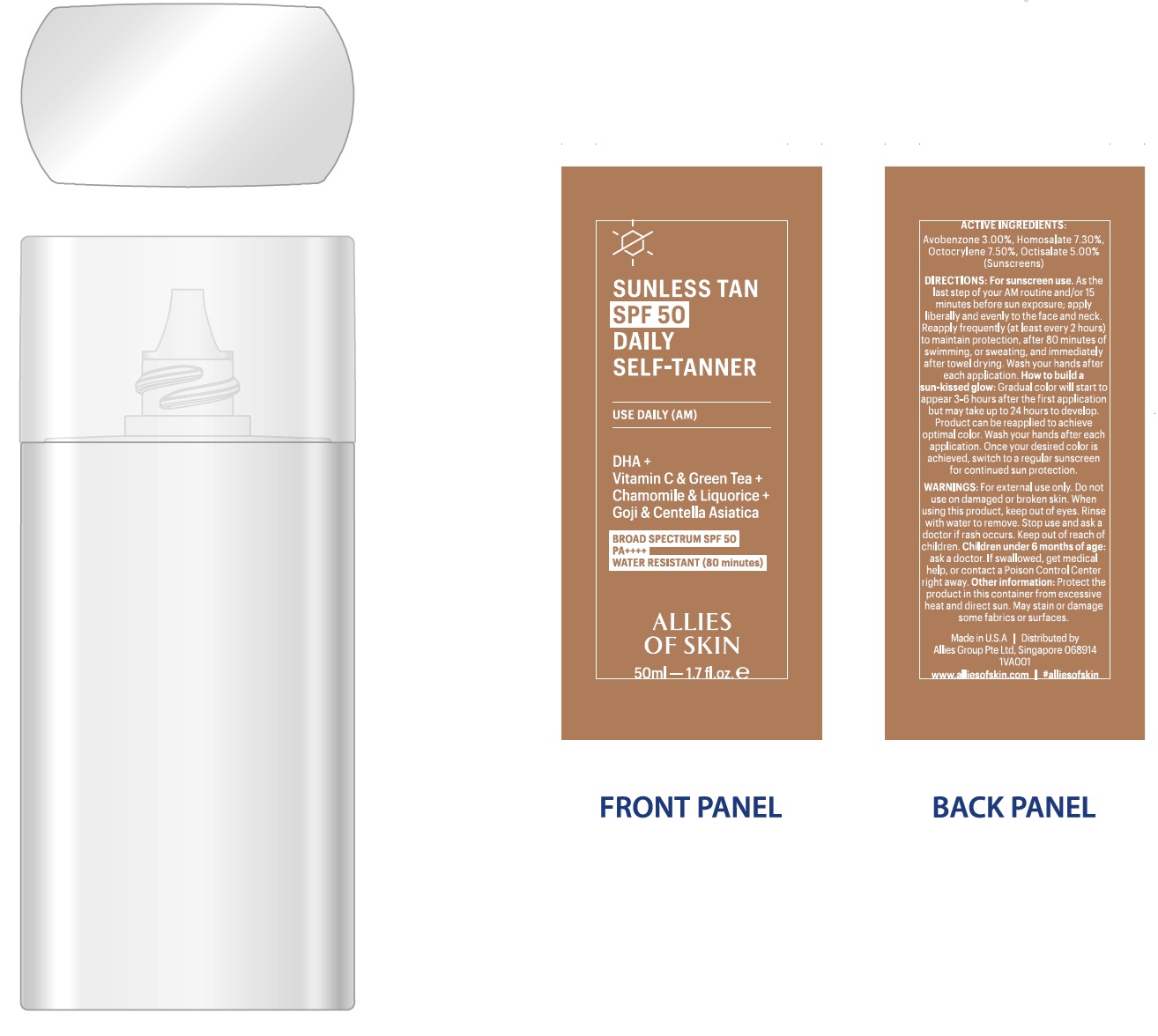 DRUG LABEL: Allies of Skin Sunless Tan SPF 50 Daily Self Tanner
NDC: 83852-543 | Form: LIQUID
Manufacturer: ALLIES GROUP PTE. LTD.
Category: otc | Type: HUMAN OTC DRUG LABEL
Date: 20250107

ACTIVE INGREDIENTS: AVOBENZONE 30 mg/1 mL; HOMOSALATE 73 mg/1 mL; OCTOCRYLENE 75 mg/1 mL; OCTISALATE 50 mg/1 mL
INACTIVE INGREDIENTS: ALOE VERA LEAF; ASCORBIC ACID; LEVOMENOL; BUTYLOCTYL SALICYLATE; ALKYL (C12-15) BENZOATE; C9-12 ALKANE; GREEN TEA LEAF; MEDIUM-CHAIN TRIGLYCERIDES; CENTELLA ASIATICA TRITERPENOIDS; CHAMOMILE; CITRIC ACID MONOHYDRATE; DAUCUS CAROTA SUBSP. SATIVUS SEED; DIHYDROXYACETONE; DIMETHICONE/BIS-ISOBUTYL PPG-20 CROSSPOLYMER; DODECANE; ETHYLHEXYLGLYCERIN; GLYCERIN; GLYCERYL STEARATE CITRATE; GLYCERYL STEARATE SE; GLYCYRRHIZA GLABRA; SUNFLOWER OIL; ISODODECANE; LYCIUM BARBARUM FRUIT; MAGNESIUM ALUMINUM SILICATE; OCTYLDODECYL NEOPENTANOATE; PHENOXYETHANOL; POLYSORBATE 20; POTASSIUM CETYL PHOSPHATE; PROPANEDIOL; POMEGRANATE; HYALURONATE SODIUM; SODIUM METABISULFITE; SODIUM STEAROYL GLUTAMATE; .ALPHA.-TOCOPHEROL ACETATE; LOWBUSH BLUEBERRY; GRAPE SEED OIL; WATER; XANTHAN GUM

Allies of Skin Sunless Tan SPF-50 Daily Self-Tanner

Active Ingredients

Avobenzone 3.00%

Homosalate 7.30%

Octocrylene 7.50%

Octisalate 5.00%

Purpose

Sunscreen

Uses:

- Helps prevent sunburn.
- Higher SPF gives more sunburn protection.
- If used as directed with other sun protection measures (see Directions), decreases the risk of skin cancer and early skin aging caused by the sun.

Warnings:

For external use only

Do not use

- on damaged or broken skin.

When using this product

- keep out of eyes. Rinse with water to remove.

Stop use and ask a doctor if

- rash or irritation develops and lasts.

Keep out of reach of children.

If swallowed, get medical help or contact a Poison Control Center right away.

If pregnant or breast-feeding,

ask a health professional before use.

Directions:

- Apply liberally 15 minutes before sun exposure and as needed.
- Children under 6 months of age: ask a doctor.
- Reapply:
- after 80 minutes of swimming or sweating
- immediately after towel drying
- at least every 2 hours
- Sun Protection Measures: Spending time in the sun increases your risk of skin cancer and early skin aging. To decrease the risk, regularly use a sunscreen with broad spectrum SPF of 15 or higher and other sun protection measures including:
- Limit time in the sun, especially from 10 a.m. - 2 p.m.
- Wear long-sleeved shirts, pants, hats, and sunglasses.

Other Information:

- Protect the product in this container from excessive heat and direct sun.
- May stain or damage some fabrics or surfaces.

Inactive Ingredients:

Aloe Barbadensis Leaf Juice, Ascorbic Acid, Bisabolol, Butyloctyl Salicylate, C12-15 Alkyl Benzoate, C9-12 Alkane, Camellia Sinensis Leaf Extract, Caprylic/Capric Triglyceride, Capryloyl Glycerin/Sebacic Acid Copolymer, Centella Asiatica Extract, Chamomilla Recutita (Matricaria) Flower Extract, Citric Acid, Daucus Carota Sativa (Carrot) Seed Extract, Dihydroxyacetone, Dimethicone/Bis-Isobutyl PPG-20 Crosspolymer, Dodecane, Ethyl Vanillin, Ethylhexylglycerin, Glycerin, Glyceryl Stearate Citrate, Glyceryl Stearate SE, Glycyrrhiza Glabra (Licorice) Root Extract, Helianthus Annuus (Sunflower) Seed Oil, Isododecane, Lactobacillus Ferment, Lycium Barbarum Fruit Extract, Magnesium Aluminum Silicate, Octyldodecyl Neopentanoate, Phenoxyethanol, Polysorbate 20, Potassium Cetyl Phosphate, Propanediol, Punica Granatum Fruit Extract, Sodium Hyaluronate, Sodium Metabisulfite, Sodium Stearoyl Glutamate, Tocopheryl Acetate, Vaccinium Angustifolium (Blueberry) Fruit Extract, Vitis Vinifera (Grape) Seed Oil, Water (Aqua), Xanthan Gum